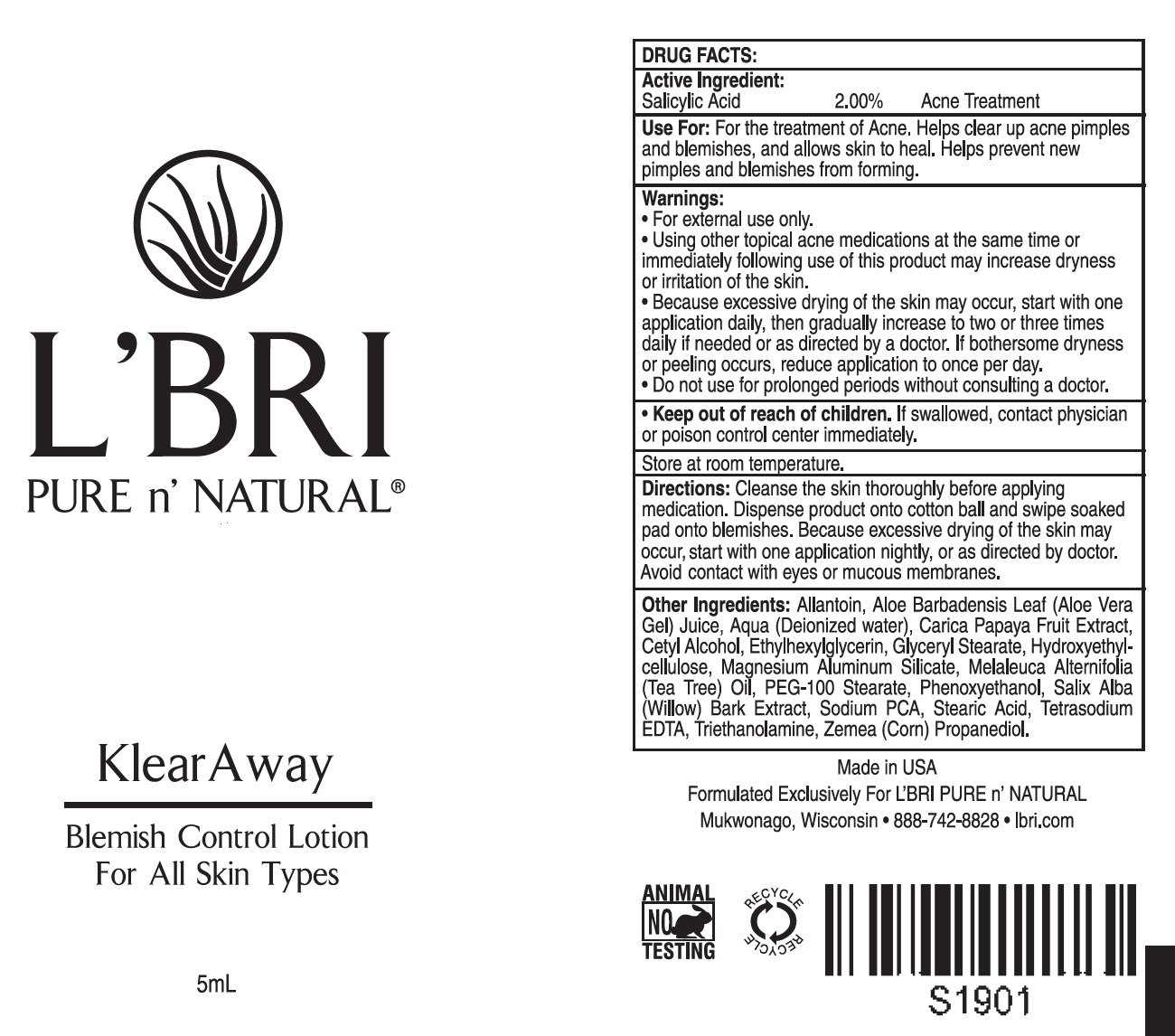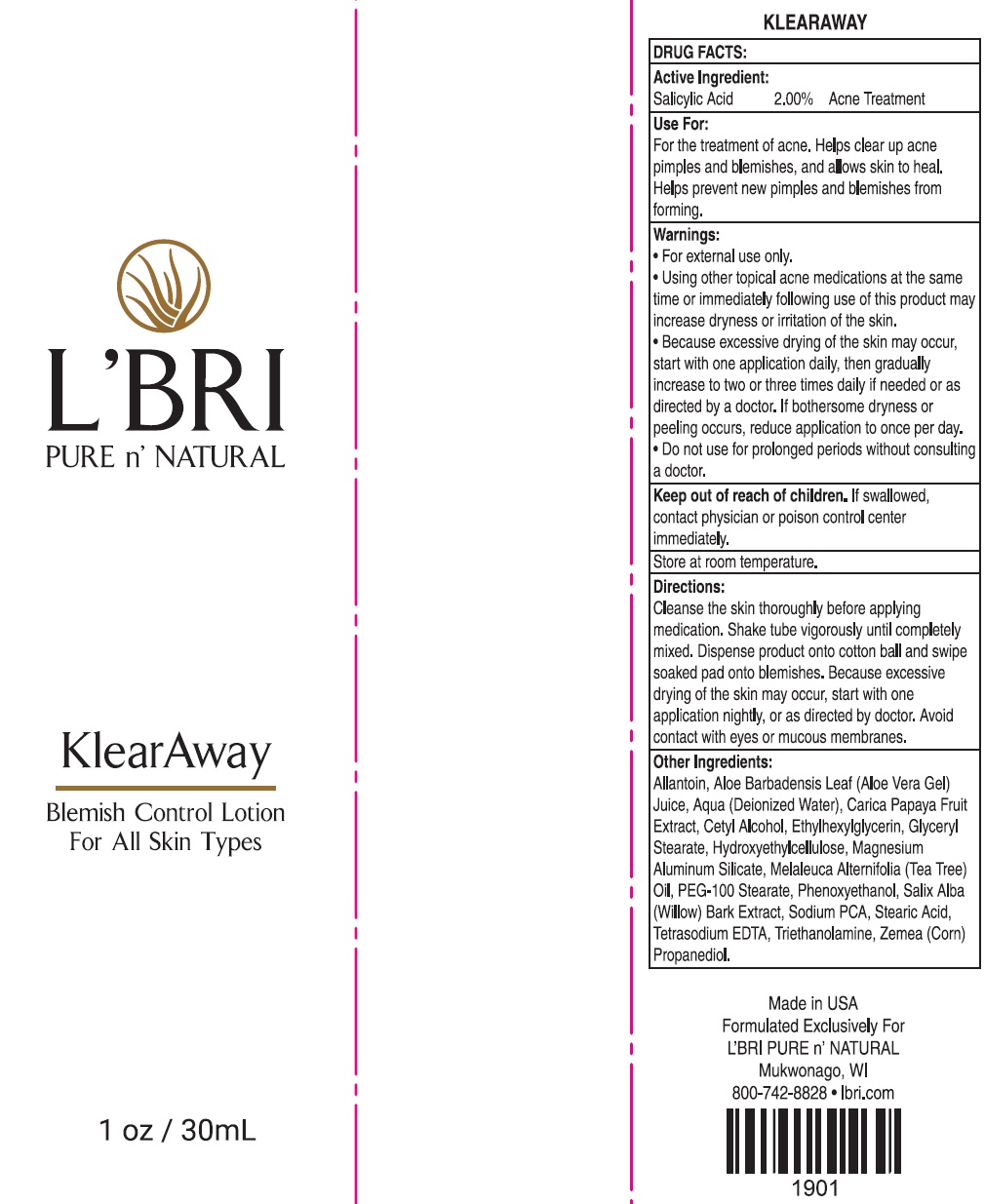 DRUG LABEL: LBRI PURE n NATURAL KlearAway
NDC: 71238-464 | Form: LOTION
Manufacturer: L'BRI Health & Beauty
Category: otc | Type: HUMAN OTC DRUG LABEL
Date: 20240222

ACTIVE INGREDIENTS: SALICYLIC ACID 20 mg/1 mL
INACTIVE INGREDIENTS: ALLANTOIN; ALOE VERA LEAF; WATER; CETYL ALCOHOL; ETHYLHEXYLGLYCERIN; GLYCERYL MONOSTEARATE; HYDROXYETHYL CELLULOSE, UNSPECIFIED; MAGNESIUM ALUMINUM SILICATE; TEA TREE OIL; PEG-100 STEARATE; PHENOXYETHANOL; SALIX ALBA BARK; SODIUM PYRROLIDONE CARBOXYLATE; STEARIC ACID; EDETATE SODIUM; TROLAMINE; CORN

L'BRI PURE n' NATURAL KlearAway

Active Ingredient:

Salicylic Acid 2.00%

PURPOSE

Acne Treatment

Use For:

For the treatment of Acne. Helps clear up acne pimples and blemishes, and allows skin to heal. Helps prevent new pimples and blemishes from forming.

Warnings:

- For external use only.
- Using other topical acne medications at the same time or immidiately following use of this product may increase dryness or irritation of the skin.
- Because excessive drying of the skin may occure, start with one application daily, then gradually increase to two or three times daily if needed or as directed by a doctor. If botheraome dryness or peeling occures, reduce aplpication to once per day.
- Do not use for prolonged periods without consulting a doctor.

Keep out of reach of children.

If swallowed, contact physician or poison control center immediately.

Store at room temparature.

Directions:

Cleanse the skin thoroughly before applying medication. Dispense product onto cotton ball snd swipe soaked pad onto blemishes. Because excessive drying of the skin may occure, start with one application nightly, or as directed by doctor. Aviod contact with eyes or mucous membranes.

Other Ingredients:

Allantoin, Aloe Barbadensis Leaf (Aloe Vera Gel) Juice, Aqua (Deionized water), Carica Papaya Fruit Extract, Cetyl Alcohol, Ethylhexylglycerin, Glyceryl Stearate, Hydroxyethylcellulose, Magnesium Aluminum Silicate, Melaleuca Alternifolia (Tea Tree) Oil, PEG-100 Stearate, Phenoxyethanol, Salix Alba (Willow) Bark Extract, Sodium PCA, Stearic Acid, Tetrasodium EDTA, Triethanolamine, Zemea (Corn) Propanediol.